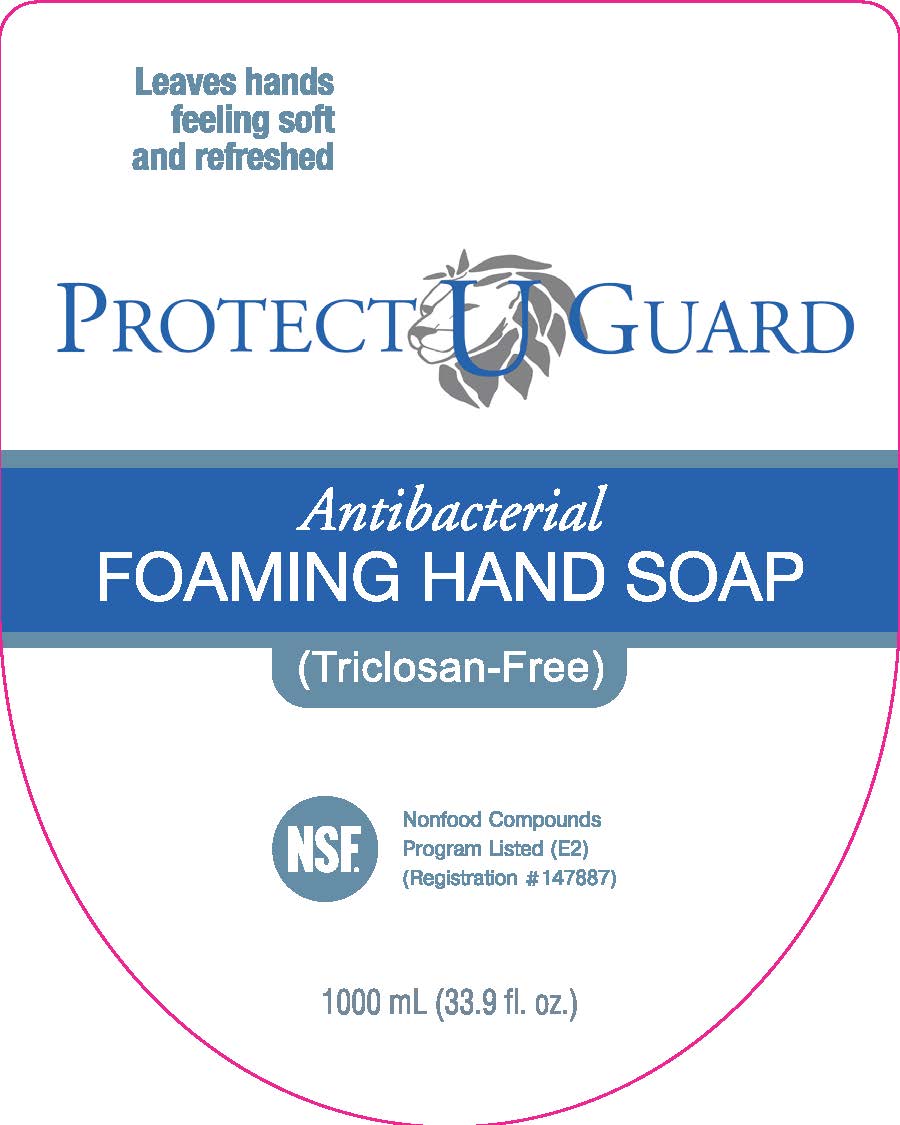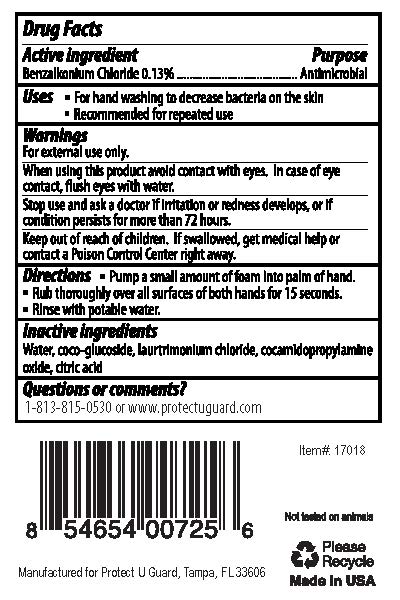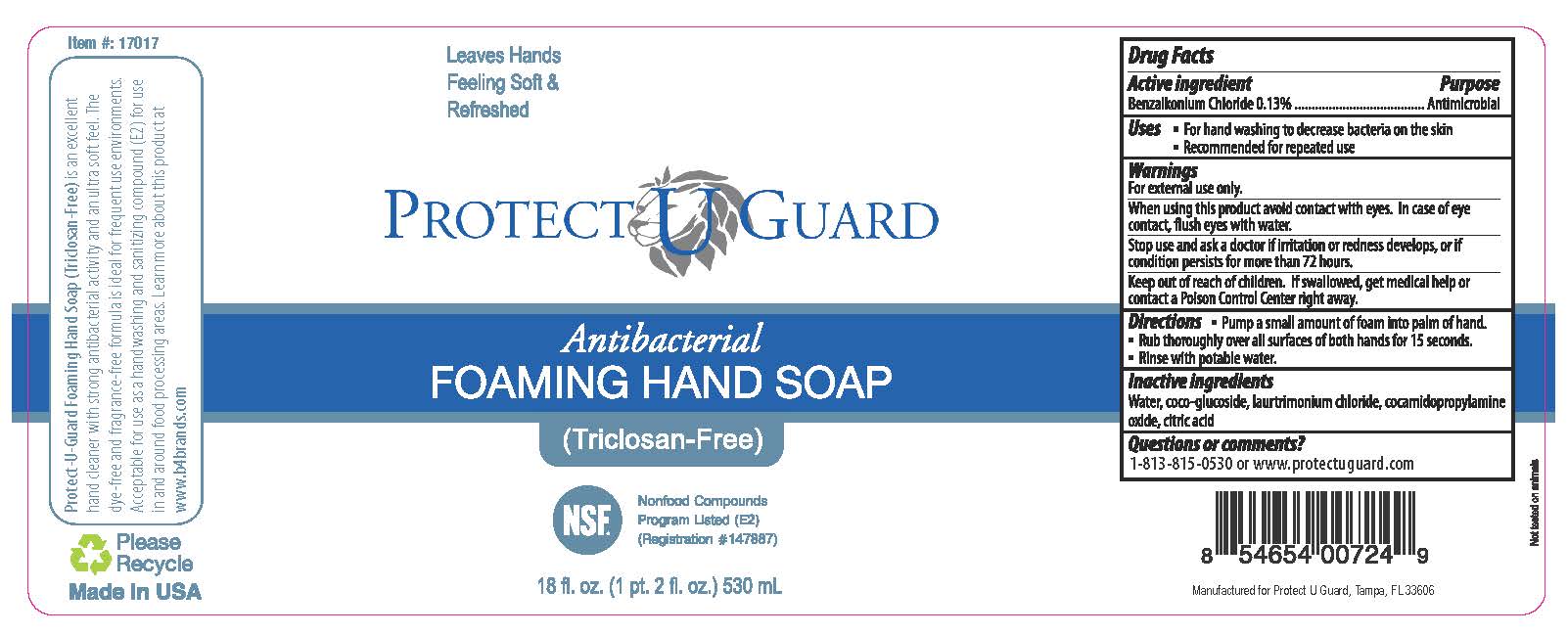 DRUG LABEL: Protect U Guard Antibacterial Foaming
NDC: 71788-346 | Form: LIQUID
Manufacturer: Protect U Guard, LLC
Category: otc | Type: HUMAN OTC DRUG LABEL
Date: 20200324

ACTIVE INGREDIENTS: BENZALKONIUM CHLORIDE 0.1 g/100 mL
INACTIVE INGREDIENTS: WATER; GLYCERIN; LAURAMINE OXIDE; PEG-120 METHYL GLUCOSE DIOLEATE

Active Ingredient

Benzalkonium Chloride 0.13%

Purpose

Antimicrobial

Uses

For Hand washing to decrease bacteria on the skin

Recommended for repeated use

Warnings

For External use only.

When using this product avoid contact with eyes. In case of eye contact, flush eyes with water.

Stop use and ask a doctor if irritation or redness develops, or if condition persists for more than 72 hours.

Keep out of reach of children. If swallowed, get medical help or contact a Poison Control Center right away.

When using this product avoid contact with eyes. In case of eye contact, flush eyes with water.

Stop use and ask a doctor if irritation or redness develops, or if condition persists for more than 72 hours.

Keep out of reach of children. If swallowed, get medical help or contact a Poison Control Center right away.

Directions

Pump a small amount of foam into palm of hand.

Rub thoroughly over all surfaces of both hands for 15 seconds.

Rinse with potable water.

Inactive ingredients

Water, coco-glucoside, laurtrimonium chloride, cocamidopropylamine oxide, citric acid

Questions or comments?

1-813-815-0530 or www.protectuguard.com